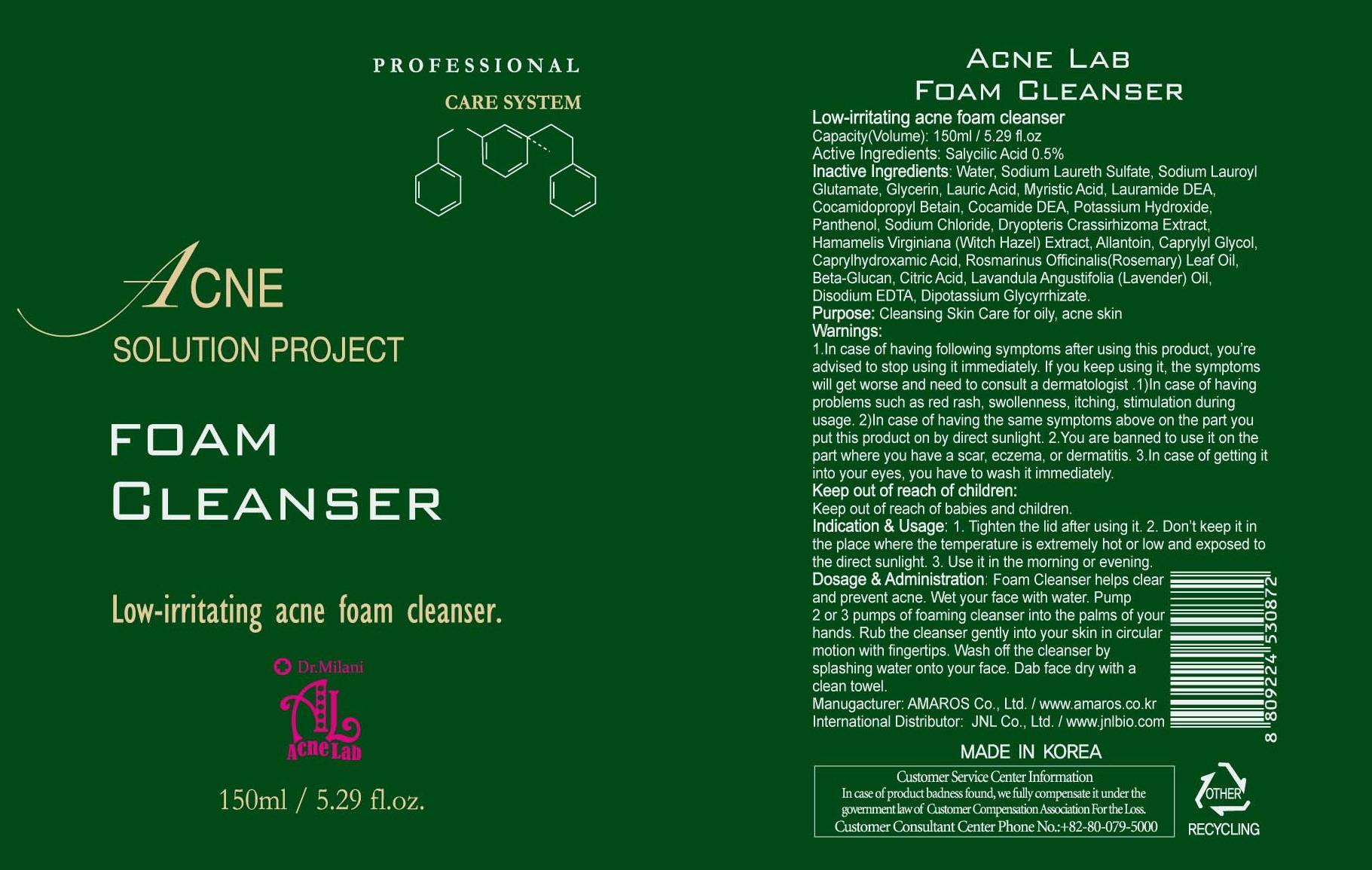 DRUG LABEL: Acne Lab Foam Cleanser
NDC: 60899-080 | Form: LIQUID
Manufacturer: AMAROS CO., LTD.
Category: otc | Type: HUMAN OTC DRUG LABEL
Date: 20190411

ACTIVE INGREDIENTS: Salicylic acid 0.75 mg/150 mL
INACTIVE INGREDIENTS: Water; Glycerin

ACTIVE INGREDIENT

Active Ingredients: Salicylic acid 0.5%

INACTIVE INGREDIENT

Inactive Ingredients: Water, Sodium Laureth Sulfate, Sodium Lauroyl Glutamate, Glycerin, Lauric Acid, Myristic Acid, Lauramide DEA, Cocamidopropyl Betain, Cocamide DEA, Potassium Hydroxide, Panthenol, Sodium Chloride, Dryopteris Crassirhizoma Extract, Hamamelis Virginiana (Witch Hazel) Extract, Allantoin, Caprylyl Glycol, Caprylhydroxamic Acid, Rosmarinus Officinalis(Rosemary) Leaf Oil, Beta-Glucan, Citric Acid, Lavandula Angustifolia (Lavender) Oil, Disodium EDTA, Dipotassium Glycyrrhizate.

PURPOSE

Purpose: Cleansing Skin Care for oily, acne skin

WARNINGS

Warnings: 1. In case of having following symptoms after using this product, you're advised to stop using it immediately. If you keep using it, the symptoms will get worse and need to consult a dermatologist. 1) In case of having problems such as red rash, swollenness, itching, stimulation during usage. 2) In case of having the same symptoms above on the part you put this product on by direct sunlight. 2. You are banned to use it on the part where you have a scar, eczema, or dermatitis. 3. In case of getting it into your eyes, you have to wash it immediately.

Keep out of reach of children: Keep out of reach of babies and children.

INDICATIONS AND USAGE

Indication and Usage: 1. Tighten the lid after using it. 2. Don't keep it in the place where the temperature is extremely hot or low and exposed to the direct sunlight. 3. Use it in the morning or evening.

Dosage and Administration: Foam Cleansing helps clear and prevent acne. Wet your face with water. Pump 2 or 3 pumps of foaming cleanser into the palms of your hands. Rub the cleanser gently into your skin in circular motion with fingertips. Wash off the cleanser by splashing water onto your face. Dab face dry with a clean towel.